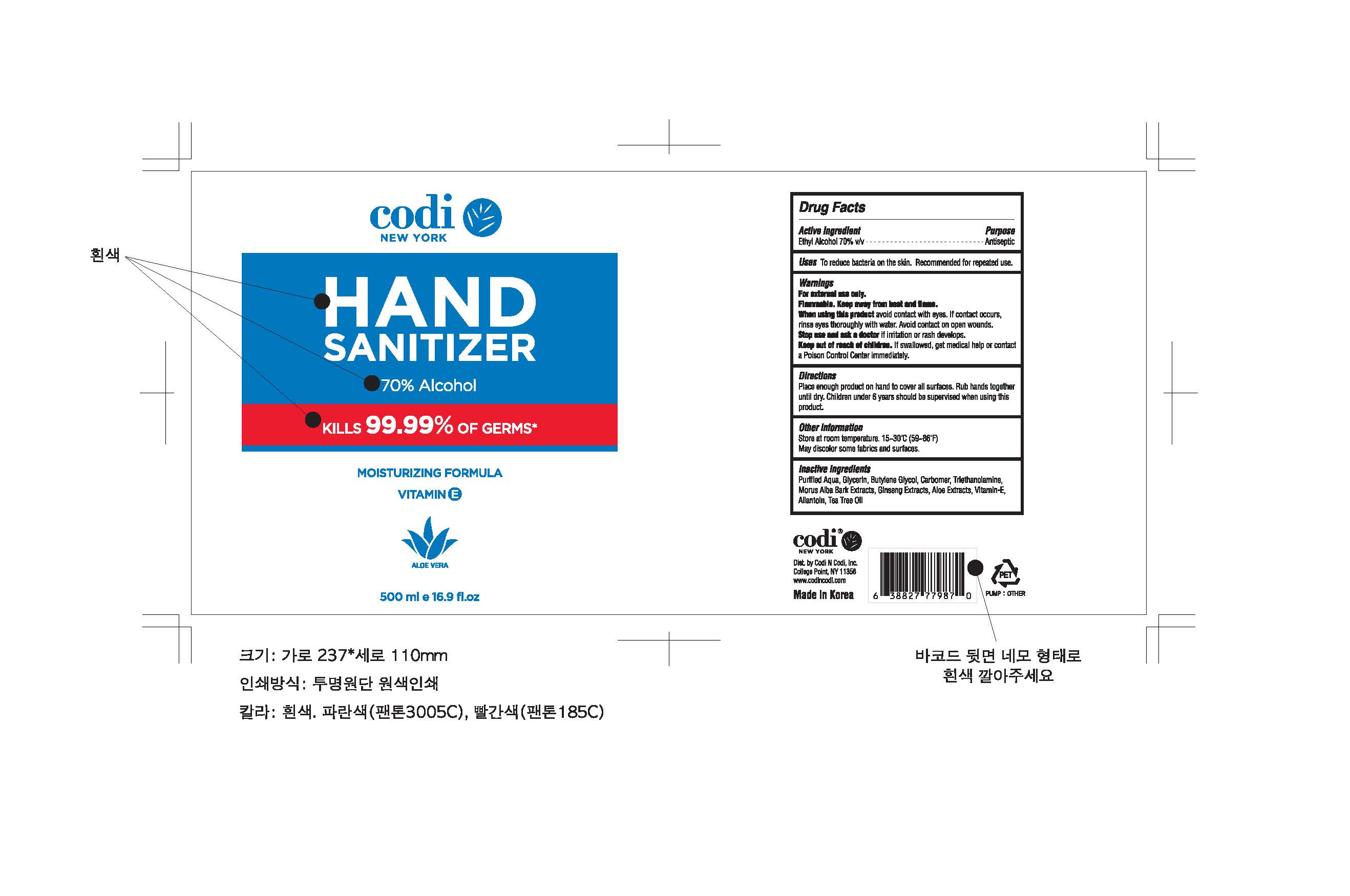 DRUG LABEL: Codi HAND SANITIZER
NDC: 78296-0001 | Form: GEL
Manufacturer: YOUSU trading
Category: otc | Type: HUMAN OTC DRUG LABEL
Date: 20200526

ACTIVE INGREDIENTS: ALCOHOL 350 mL/500 mL
INACTIVE INGREDIENTS: GLYCERIN; WATER; CARBOMER HOMOPOLYMER, UNSPECIFIED TYPE; BUTYLENE GLYCOL; ALOE

Drug Facts

ACTIVE INGREDIENT

Alcohol

INACTIVE INGREDIENT

Water

Glycerin

Butylene Glycol

Carbomer

Triethanolamine

Mulberry Root Extract

Ginseng Extract

Aloe Extract

Allantoin

Tocopheryl Acetate

Tea Tree Oil

PURPOSE

Antiseptic

KEEP OUT OF REACH OF THE CHILDREN

INDICATIONS AND USAGE

For the external use only

WARNINGS

For external use only.

Flammable, keep away from fire or flame.

When using this product keep out of eyes. If contact with eyes occurs, rinse promptly and thoroughly with water.

Stop use and ask a doctor if significant irritation or sensitization develops.

Keep out of reach of children. If swallowed, get medical help or contact a Poison Control Center right away.

DOSAGE AND ADMINISTRATION

Place enough product on hand to cover all surfaces. Rub hands together until dry. Children under 6 years should be supervised when using this product.